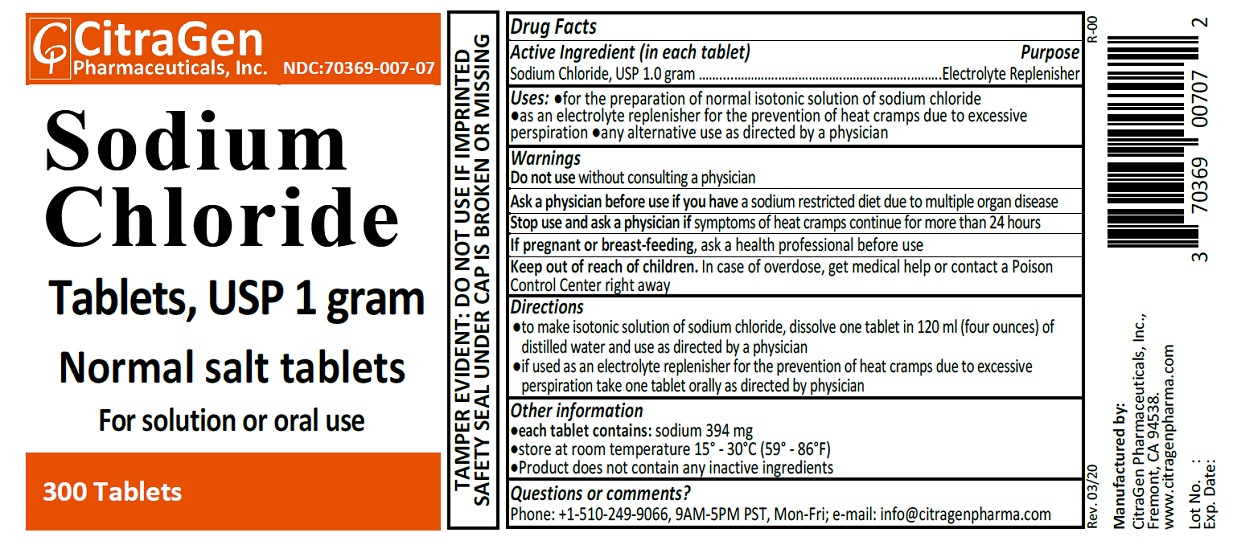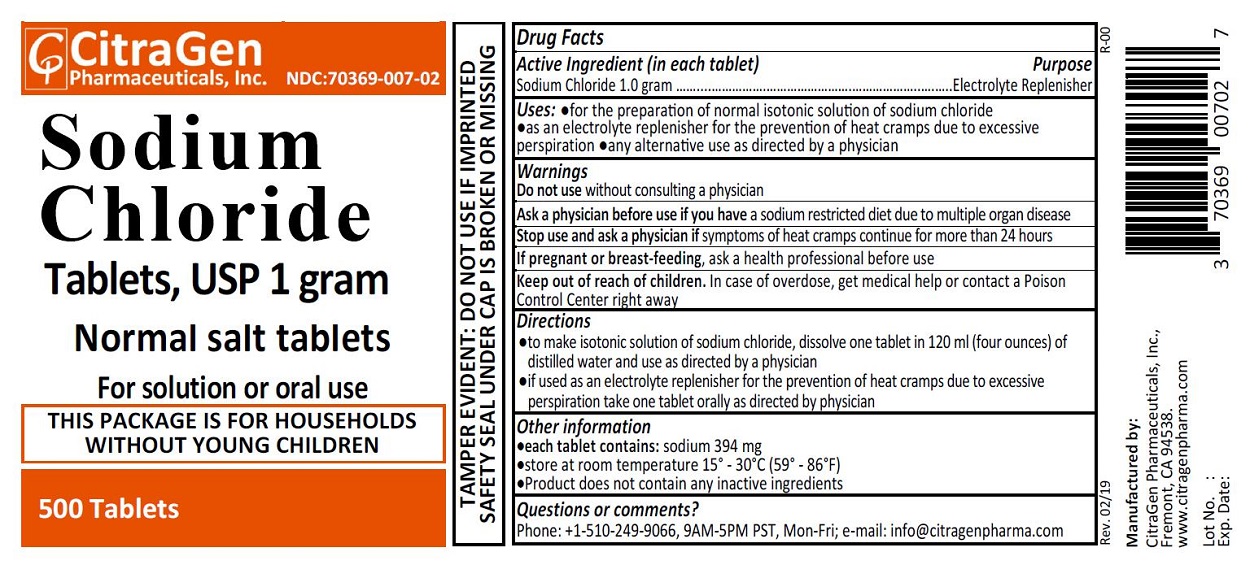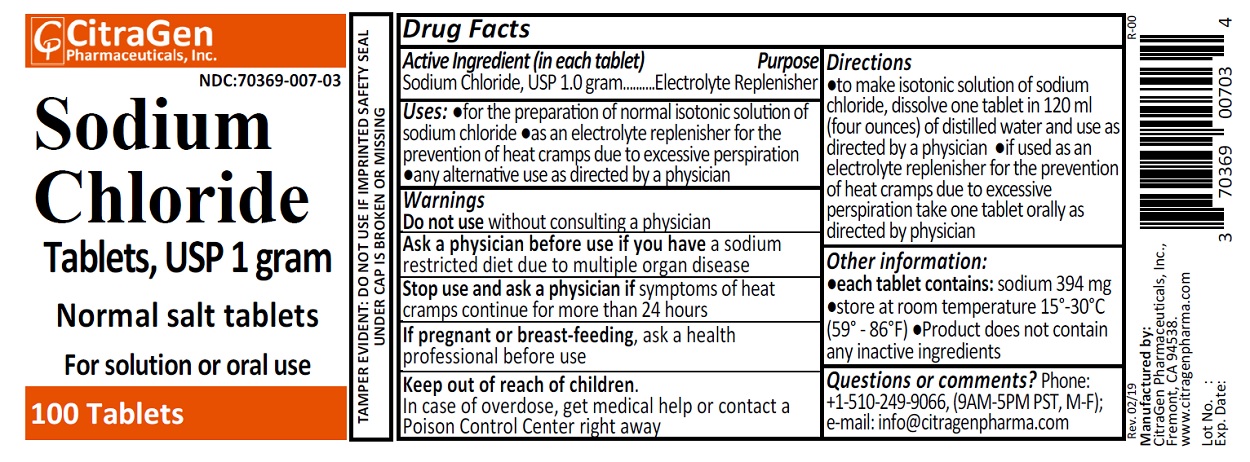 DRUG LABEL: Sodium Chloride
NDC: 70369-007 | Form: TABLET
Manufacturer: Citragen Pharmaceuticals Inc
Category: otc | Type: HUMAN OTC DRUG LABEL
Date: 20250130

ACTIVE INGREDIENTS: SODIUM CHLORIDE 1 g/1 1

Sodium Chloride Tablets, USP

Drug Facts

Active ingredient (in each tablet)

Sodium Chloride, USP 1.0 gram

Purpose

Electrolyte Replenisher

Uses

- for the preparation of normal isotonic solution of sodium chloride
- as an electrolyte replenisher for the prevention of heat cramps due to excessive perspiration
- any alternative use as directed by a physician

Warnings

Do not use without consulting a physician

ASK DOCTOR

Ask a physician before use if you have a sodium restricted diet due to multiple organ diseases

Stop use and ask a physician if symptoms of heat cramps continue for more than 24 hours.

PREGNANCY OR BREAST FEEDING

If pregnant or breast-feeding, ask a health professional before use.

OVERDOSAGE

In case of overdose, get medical help or contact a Poison Control Center right away.

Directions

- to make isontonic solution of sodium chloride, dissolve one tablet in 120 ml (four ounces) of distilled water and use as directed by a physician.
- if used as an electrolyte replenisher for the prevention of heat cramps due to excessive perspiration take one tablet orally as directed by your physician.

Other information:

- each tablet contains: sodium 394 mg
- store at room temperature 15°-30°C (59°-86°F)
- product does not contain any inactive ingredients

Questions or comments?

Phone: +1-510-249-9066 (9AM-5PM PST, Mon-Fri); e-mail: info@citragenpharma.com

TAMPER EVIDENT: DO NOT USE IF IMPRINTED SAFETY SEAL UNDER CAP IS BROKEN OR MISSING

Manufactured by:

CitraGen Pharmaceuticals, Inc.,
Fremont, CA 94538.

www.citragenpharma.com

Rev. 02/19 R-00

PACKAGE LABEL

CitraGen Pharmaceuticals, Inc.

NDC: 70369‐007‐02

Sodium Chloride Tablets, USP 1 gram

Normal salt tablets

For solution or oral use
500 Tablets

THIS PACKAGE IS FOR HOUSEHOLDS WITHOUT YOUNG CHILDREN

PACKAGE LABEL

CitraGen Pharmaceuticals, Inc.

NDC: 70369‐007‐03

Sodium Chloride Tablets, USP 1 gram

Normal salt tablets

For solution or oral use
100 Tablets

PACKAGE LABEL

CitraGen Pharmaceuticals, Inc.

NDC: 70369‐007‐07

Sodium Chloride Tablets, USP 1 gram

Normal salt tablets

For solution or oral use
300 Tablets